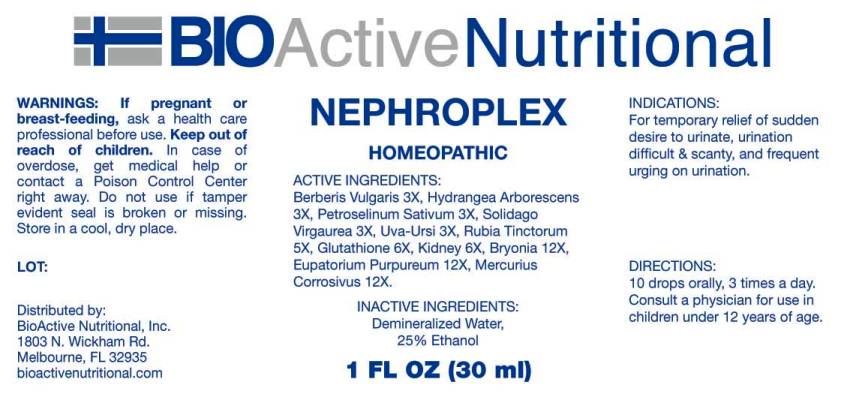 DRUG LABEL: Nephroplex
NDC: 43857-0136 | Form: LIQUID
Manufacturer: BioActive Nutritional, Inc.
Category: homeopathic | Type: HUMAN OTC DRUG LABEL
Date: 20160913

ACTIVE INGREDIENTS: BERBERIS VULGARIS ROOT BARK 3 [hp_X]/1 mL; HYDRANGEA ARBORESCENS ROOT 3 [hp_X]/1 mL; PETROSELINUM CRISPUM 3 [hp_X]/1 mL; SOLIDAGO VIRGAUREA FLOWERING TOP 3 [hp_X]/1 mL; ARCTOSTAPHYLOS UVA-URSI LEAF 3 [hp_X]/1 mL; RUBIA TINCTORUM ROOT 5 [hp_X]/1 mL; GLUTATHIONE 6 [hp_X]/1 mL; PORK KIDNEY 6 [hp_X]/1 mL; BRYONIA ALBA ROOT 12 [hp_X]/1 mL; EUTROCHIUM PURPUREUM ROOT 12 [hp_X]/1 mL; MERCURIC CHLORIDE 12 [hp_X]/1 mL
INACTIVE INGREDIENTS: WATER; ALCOHOL

Drug Facts:

ACTIVE INGERDIENTS

Berberis Vulgaris 3X, Hydrangea Arborescens 3X, Petroselinum Sativum 3X, Solidago Virgaurea 3X, Uva Ursi 3X, Rubia Tinctorum 5X, Glutathione 6X, Kidney (Suis) 6X, Bryonia 12X, Eupatorium Purpureum 12X, Mercurius Corrosivus 12X.

INDICATIONS

For temporary relief of sudden desire to urinate, urination difficult and scanty, and frequent urging on urination.

WARNINGS

If pregnant or breast-feeding, ask a health care professional before use.

Keep out of reach of children. In case of overdose, get medical help or contact a Poison Control Center right away.

Do not use if tamper evident seal is broken or missing.

Store in cool, dry place.

DIRECTIONS

10 drops orally, 3 times a day. Consult a physician for use in children under 12 years of age.

INACTIVE INGREDIENTS

Demineralized Water, 25% Ethanol.

Keep out of reach of children. In case of overdose, get medical help or contact a Poison Control Center right away.

INDICATIONS:

For temporary relief of sudden desire to urinate, urination difficult and scanty, and frequent urging on urination.

QUESTIONS

Distributed by:
BioActive Nutritional, Inc.
1803 N. Wickham Rd.
Melbourne, FL 32935
bioactivenutritional.com

PACKAGE LABEL DISPLAY:

BIOActive Nutritional

NEPHROPLEX

HOMEOPATHIC

1 FL OZ (30 ml)